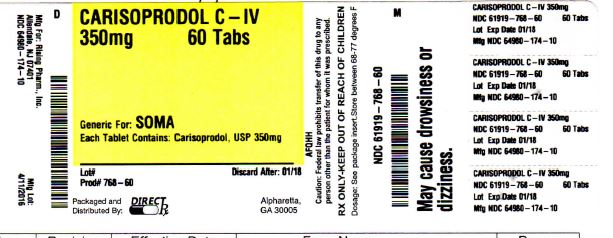 DRUG LABEL: CARISOPRODOL
NDC: 61919-768 | Form: TABLET
Manufacturer: DIRECT RX
Category: prescription | Type: HUMAN PRESCRIPTION DRUG LABEL
Date: 20160413
DEA Schedule: CIV

ACTIVE INGREDIENTS: CARISOPRODOL 350 mg/1 1
INACTIVE INGREDIENTS: HYDROXYPROPYL CELLULOSE (TYPE H); ANHYDROUS LACTOSE; STARCH, CORN; MAGNESIUM STEARATE; SODIUM STARCH GLYCOLATE TYPE A POTATO; CELLULOSE, MICROCRYSTALLINE; SODIUM LAURYL SULFATE

CARISOPRODOL C-IV 350 mg 60 TABS